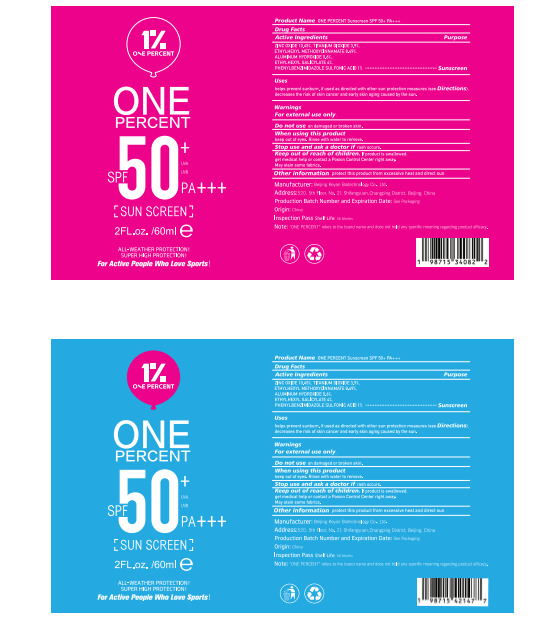 DRUG LABEL: ONE PERCENT Sunscreen
NDC: 85176-001 | Form: CREAM
Manufacturer: Beijing Keyan Biotechnology Co., Ltd.
Category: otc | Type: HUMAN OTC DRUG LABEL
Date: 20250205

ACTIVE INGREDIENTS: ETHYLHEXYL METHOXYCINNAMATE 8.49405 g/100 mL; TITANIUM DIOXIDE 3.9 g/100 mL; ALUMINUM HYDROXIDE 0.6 g/100 mL; ETHYLHEXYL SALICYLATE 4 g/100 mL; PHENYLBENZIMIDAZOLE SULFONIC ACID 1 g/100 mL; ZINC OXIDE 10.45 g/100 mL
INACTIVE INGREDIENTS: SILICA; DISTEARDIMONIUM HECTORITE; BIS-ETHYLHEXYLOXYPHENOL METHOXYPHENYL TRIAZINE; TRIMETHYLSILOXYSILICATE (M/Q 0.8-1.0); PHENOXYETHANOL; STEARIC ACID; WATER; CYCLOPENTASILOXANE; TRIETHOXYCAPRYLYLSILANE; DIMETHICONE; POLYMETHYLSILSESQUIOXANE; SODIUM CHLORIDE; GLYCERIN; TROLAMINE SALICYLATE; BHT; LAURYL PEG-9 POLYDIMETHYLSILOXYETHYL DIMETHICONE; ETHYLHEXYLGLYCERIN; ISODODECANE; BUTYLENE GLYCOL; PHENYL TRIMETHICONE; DEXTRIN PALMITATE (CORN; 20000 MW); PROPYLENE CARBONATE; DIETHYLAMINO HYDROXYBENZOYL HEXYL BENZOATE

85176-001

Active Ingredient(s)

ZINC OXIDE 10.45%

ETHYLHEXYL METHOXYCINNAMATE 8.49405%

TITANIUM DIOXIDE 3.9%

ALUMINUM HYDROXIDE 0.6%

ETHYLHEXYL SALICYLATE 4%

PHENYLBENZIMIDAZOLE SULFONIC ACID 1%

Purpose

Sunscreen

Use

helps prevent sunburn. if used as directed with other sun protection measures (see Directions).
decreases the risk of skin cancer and early skin aging caused by the sun.

Warnings

For external use only.

Do not use on damaged or broken skin.

When using this product
keep out of eyes. Rinse with water to remove.

Stop use and ask a doctor if rash occurs.

Keep out of reach of children. If product is swallowed, get medical help or contact a Posion Control Center right away.
May stain some fabrics.

Directions

1. Clean the face
2. Moisturizing and hydrating
3. Apply sunscreen

Other information

Other information protect this product from excessive heat and direct sun

Inactive ingredients

WATER, CYCLOPENTASILOXANE, TRIETHOXYCAPRYLYLSILANE, DIMETHICONE, GLYCERIN, SODIUM CHLORIDE,

TRIETHANOLAMINE, BHT, ISODODECANE, STEARIC ACID, PHENYL TRIMETHICONE, POLYMETHYLSILSESQUIOXANE,

BUTYLENE GLYCOL, DIETHYLAMINO HYDROXYBENZOYL HEXYL BENZOATE, LAURYL PEG-9 POLYDIMETHYLSILOXYETHYL DIMETHICONE, SILICA, BIS-ETHYLHEXYLOXYPHENOL METHOXYPHENYL TRIAZINE, TRIMETHYLSILOXYSILICATE,

PHENOXYETHANOL, DISTEARDIMONIUM HECTORITE, DEXTRIN PALMITATE, PROPYLENE CARBONATE,

ETHYLHEXYLGLYCERIN